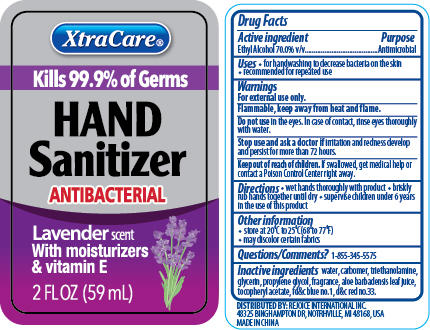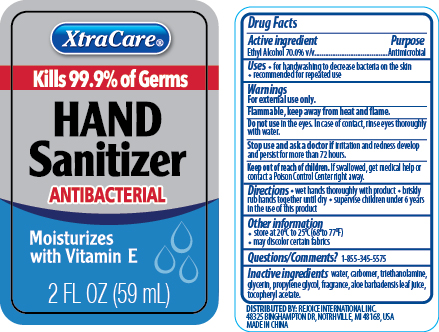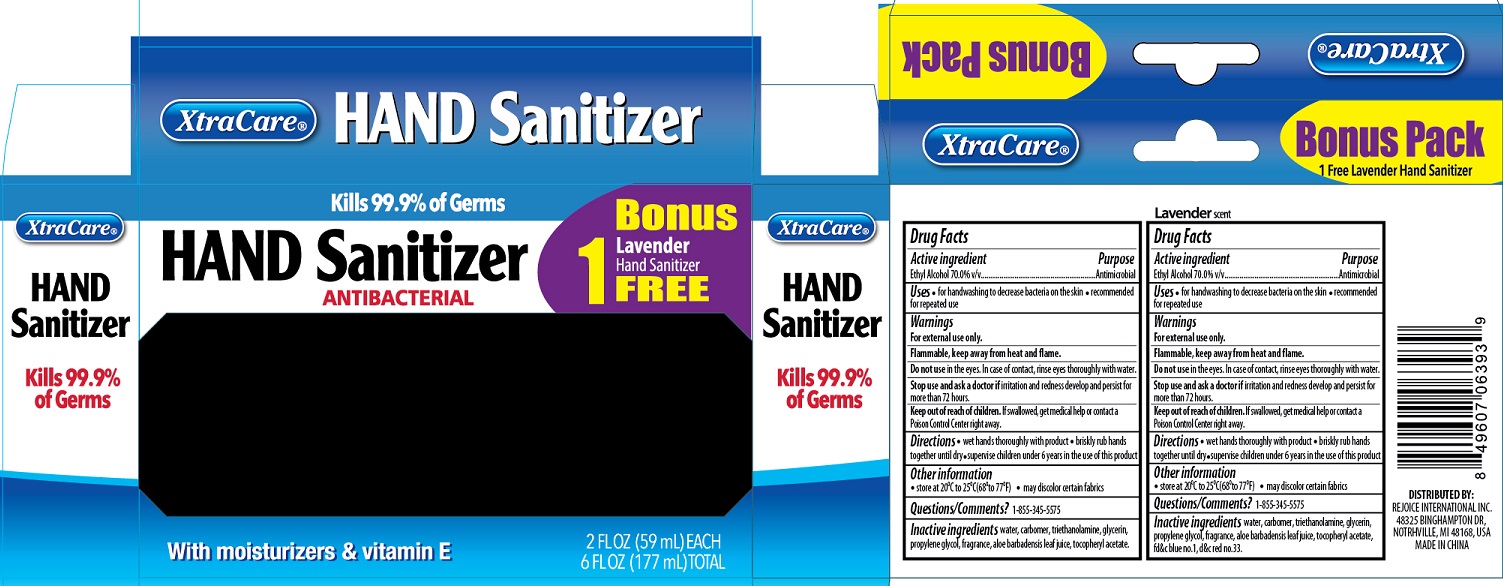 DRUG LABEL: Instant Hand Sanitizer
NDC: 57337-093 | Form: LIQUID
Manufacturer: Rejoice International Inc.
Category: otc | Type: HUMAN OTC DRUG LABEL
Date: 20250212

ACTIVE INGREDIENTS: ALCOHOL 70 mL/100 mL
INACTIVE INGREDIENTS: ALOE VERA LEAF; D&C RED NO. 33; GLYCERIN; PROPYLENE GLYCOL; .ALPHA.-TOCOPHEROL ACETATE; WATER; CARBOMER COPOLYMER TYPE A (ALLYL PENTAERYTHRITOL CROSSLINKED); TROLAMINE; FD&C BLUE NO. 1

3 pack Hand sanitizer 2oz Bonus pack

Active Ingredient

Ethyl Alcohol 70.0% v/v

PURPOSE

Antimicrobial

Keep out of reach of children. If swallowed, get medical help or contact a Poison Control Center right away.

Directions

- wet hands thoroughly with product
- briskly rub hands together until dry
- supervise children under 6 years in the use of this product

Use:

- for handwashing to decrease bacteria on the skin
- recommended for repeated use

Warnings:

For external use only.

Flammable. Keep away from heat and flame.

Do not use in the eyes. In case of contact, rinse eyes thoroughly with water.

Stop use and ask a doctor if irritation and redness develop and persist for more than 72 hours.

INACTIVE INGREDIENT

Inactive Ingredients: water, carbomer, triethanolamine, glycerin, propylene glycol, fragrance, aloe barbadensis leaf juice, tocopheryl acetate (Vitamin E), fd&c blue no. 1, D&C Red no. 33